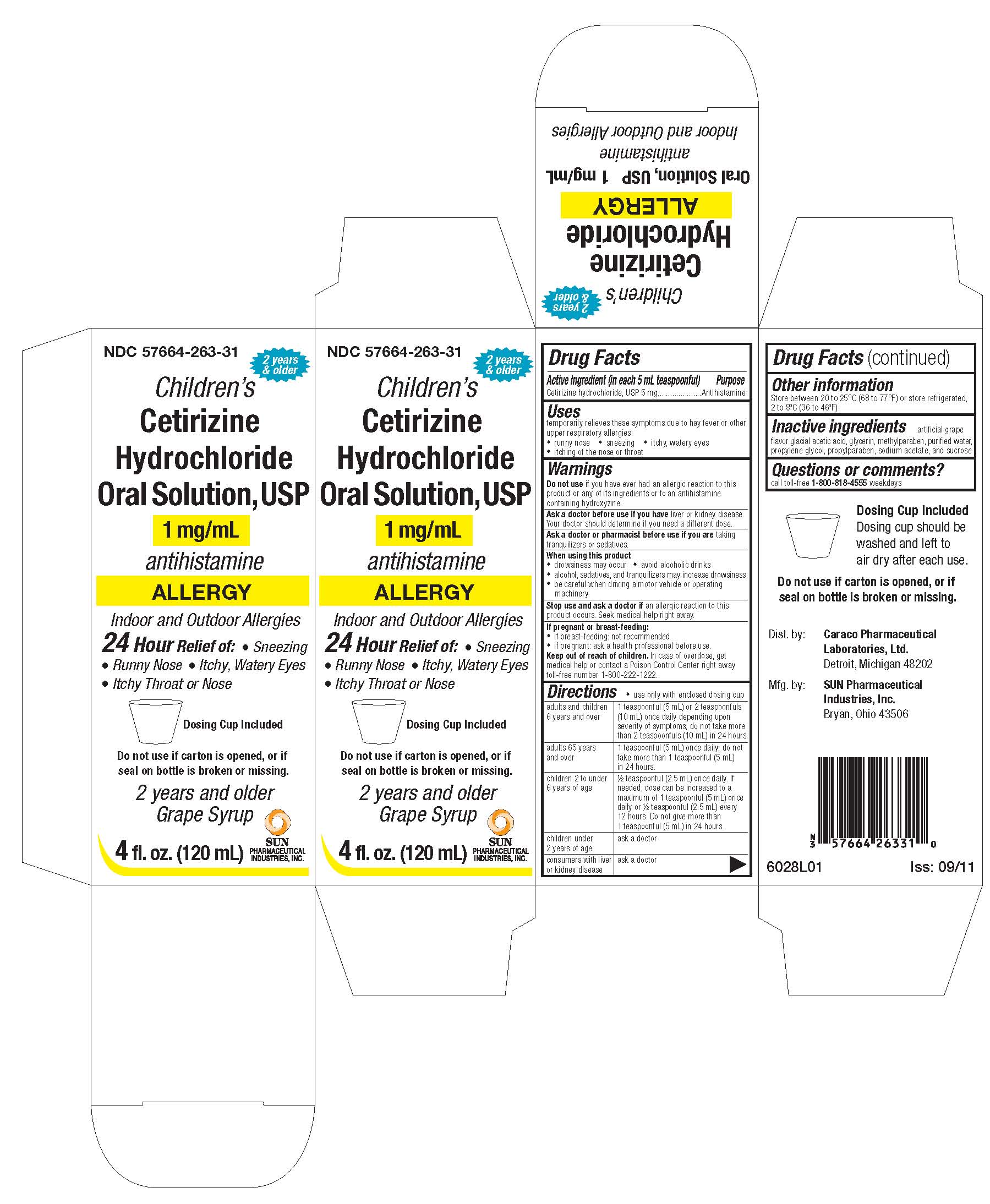 DRUG LABEL: CETIRIZINE HYDROLORIDE Allergy
NDC: 57664-263 | Form: SOLUTION
Manufacturer: Caraco Pharmaceutical Laboratories, Ltd
Category: otc | Type: Human OTC Drug Label
Date: 20111003

ACTIVE INGREDIENTS: CETIRIZINE HYDROCHLORIDE 1 mg/1 mL
INACTIVE INGREDIENTS: ACETIC ACID; GLYCERIN; METHYLPARABEN; WATER; PROPYLENE GLYCOL; PROPYLPARABEN; SODIUM ACETATE; SUCROSE

Active Ingredient (in each 5 mL teaspoonful)

Cetirizine hydrochloride, USP 5mg

Purpose

Antihistamine

Uses

temporarily relieves these symptoms due to hay fever or other upper respiratory allergies:

- runny nose
- sneezing
- itchy, watery eyes
- itching of the nose or throat

Warnings

Do not use if you have ever had an allergic reaction to this product or any of its ingredients or to an antihistamine containing hydroxyzine.

Ask a doctor before use if you have liver or kidney disease. Your doctor should determine if you need a different dose.

Ask a doctor or pharmacist before use if you are taking tranquilizers or sedatives.

When using this product

- drowsiness may occur
- avoid alcoholic drinks
- alcohol, sedatives, and tranquilizers may increase drowsiness
- be careful when driving a motor vehicle or operating machinery

Stop use and ask doctor if an allergic reaction to this product occurs. Seek medical help right away.

If pregnant or breast-feeding:

- if breast-feeding: not recommended
- if pregnant: ask a health professional before use.

Keep out of reach of children.

In case of overdose, get medical help or contact a Poison Control Center right away toll-free number 1-800-222-1222.

Directions

- use only with enclosed dosing cup

adults and children 6 years and over | 1 teaspoonful (5 mL) or 2 teaspoonfuls (10 mL) once daily depending upon severity of symptoms; do not take more than 2 teaspoonfuls (10 mL) in 24 hours.
adults 65 years and over | 1 teaspoonful (5 mL) once daily; do not take more than 1 teaspoonful (5 mL) in 24 hours.
children 2 to under 6 years of age | ½ teaspoonful (2.5 mL) once daily. If needed, dose can be increased to a maximum of 1 teaspoonful (5 mL) once daily or ½ teaspoonful (2.5 mL) every 12 hours. Do not give more than 1 teaspoonful (5 mL) in 24 hours.
children under 2 years of age | ask a doctor
consumers with liver or kidney disease | ask a doctor

Other information

Store between 20 to 25ºC (68 to 77ºF) or store refrigerated, 2 to 8ºC (36 to 46ºF)

Inactive ingredients

artificial grape flavor, glacial acetic acid, glycerin, methylparaben, purified water, propylene glycol, propylparaben, sodium acetate, and sucrose

Questions or comments?

call toll-free 1-800-818-4555 weekdays

Dosing Cup Included

Dosing cup should be washed and left to air dry after each use.

Do not use if carton is opened, or if seal on bottle is broken or missing.

Dist. by: Caraco Pharmaceutical Laboratories, Ltd.

Detroit, Michigan 48202

Mfg. by: SUN Pharmaceutical Industries, Inc.

Bryan, Ohio 43506

6028L01 Iss: 09/11

Principal Display Panel

NDC 57664-263-31
2 years & older

Children’s

Cetirizine

Hydrochloride

1mg / mL Oral Solution, USP

antihistamine

ALLERGY

Indoor and Outdoor Allergies

24 Hour Relief of

- Sneezing
- Runny Nose
- Itchy, Watery Eyes
- Itchy Throat or Nose

Dosing Cup Included

Do not use if carton is opened, or if seal on bottle is broken or missing.

2 years and older

Grape Syrup

4 fl. oz. (120 mL)